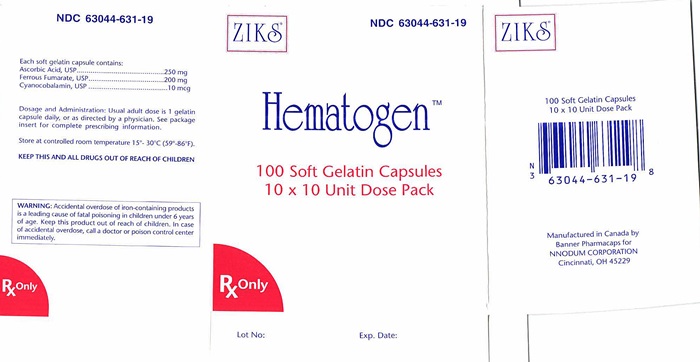 DRUG LABEL: HEMATOGEN
                        
                
                
                
                
                
                
NDC: 63044-631 | Form: CAPSULE
Manufacturer: Nnodum Pharmaceuticals
Category: prescription | Type: HUMAN PRESCRIPTION DRUG LABEL
Date: 20241228

ACTIVE INGREDIENTS: FERROUS FUMARATE 66 mg/1 1; ASCORBIC ACID 250 mg/1 1; INTRINSIC FACTOR 100 mg/1 1; CYANOCOBALAMIN 10 ug/1 1

Hematogen Softgel capsule

Ferrous fumarate (66 mg elemental iron) USP................... 200 mg

Ascorbic acid USP.................................................................. 250 mg

Desiccated stomach powder................................................... 100 mg

(Contains: Intrinsic factor),

Cyanocobalamin USP...............................................................10 mcg

DISCUSSION: The amount of elemental iron and the absorption of the iron components of commercial iron preparations vary widely. It is further established that certain "accessory components" may be included to enhance absorption and utilization of iron. Hematogen™ Capsules are formulated to provide the essential factors for a complete, versatile hematinic.

ACTIONS/CLINICAL PHARMACOLOGY

HIGH ELEMENTAL IRON CONTENT: Ferrous fumarate, used in Hematogen™ Capsules, is an organic iron complex which has the highest elemental iron content of any hematinic salt-33%. This compares with 20% for ferrous sulfate (heptahydrate) and 13% for ferrous gluconate. Hematogen™ contains 66 mg of elemental iron.

MORE COMPLETE ABSORPTION: It has been repeatedly shown that ascorbic acid, when given in sufficient amounts, can increase the absorption of ferrous iron from the gastrointestinal tract. The absorption promoting effect is mainly due to the reducing action of ascorbic acid within the gastro intestinal lumen, which helps to prevent or delay the formation of insoluble or less dissociated ferric compounds.

Iron absorption has been shown to increase sharply with increasing amounts of ascorbic acid, showing a gain in absorption of approximately 40% at 250 mg. Above 250 mg, the gain becomes insignificant, with an additional gain of only approximately 8% at 500 mg. Each Hematogen™ Capsule contains 250 mg of ascorbic acid, believed to be the optimal amount.

PROMOTES MOVEMENT OF PLASMA IRON: Ascorbic acid also plays an important role in the movement of plasma iron to storage depots in the tissues . The action, which leads to the transport of plasma iron to ferritin, presumably involves its reducing effect; converting transferrin iron from 5 the ferric to the ferrous state. There is also evidence that ascorbic acid improves iron utilization,

presumably as a further result of its reducing action , and some evidence that it may have a direct effect upon erythropoiesis. Ascorbic acid is further alleged to enhance the conversion of folic acid to a more physiologically active form, folinic acid. which would make it even more important in the 11 treatment of anemia since it would aid in the utilization of dietary folic acid.

EXCELLENT ORAL TOLERATION: Ferrous fumarate is used in Hematogen™ Capsules because it is less likely to cause the gastric disturbances so often associated with oral iron therapy. Ferrous fumarate has a low ionization constant and high solubility in the entire pH range of the gastrointestinal tract.

It does not precipitate proteins or have the astringency of more ionizable forms of iron, and does not interfere with proteolytic or diastatic activities of the digestive system. Because of excellent oral toleration, Hematogen™ Capsules can usually be administered between meals when iron absorption is maximal.

FACILITATES ABSORPTION OF VITAMIN B12 : It is now known that "Intrinsic Factor" is essential for the adequate alimentary absorption of vitamin B. The inclusion of desiccated stomach powder 12 with oral vitamin B will furnish sufficient intrinsic factor to assure absorption of the vitamin 12

only

TOXICITY: Ferrous fumarate was found to be the least toxic of three popular oral iron salts, with an oral LD50 of 630 mg/kg. In the same report, the LD50 of ferrous gluconate was reported to be 320 mg/kg and ferrous sulfate 230 mg/kg.

INDICATIONS:

For the treatment of all anemias responsive to oral iron therapy, such as hypochromic anemia associated with pregnancy, chronic or acute blood loss, dietary restriction, metabolic disease and post-surgical convalescence.

CONTRAINDICATIONS:

Hemochromatosis and hemosiderosis are contraindications to iron therapy.

WARNING: Accidental overdose of iron-containing products is a leading cause of fatal poisoning in children under 6 years of age. Keep this product out of reach of children. In case of accidental overdose, call a doctor or poison control center immediately.

ADVERSE REACTIONS:

Average capsule doses in sensitive individuals or excessive dosage may cause nausea, skin rash, vomiting, diarrhea, precordial pain, or flushing of the face or extremities.

DOSAGE AND ADMINISTRATION:

Usual adult dose is 1 soft gelatin capsule daily.

HOW SUPPLIED:

Each Red soft gelatin capsule is imprinted with "Ziks631" on one side. NDC 63044-0631-19 10 x 10, unit dose packs, in packs of 100's.

Store at controlled between temperature 15°- 30°C (59°- 86°F). Protect from direct / excessive heat 40°C (104°F). Avoid freezing.

1 BIBLIOGRAPHY: Berk, M.S. and Novich, M.A.: 'Treatment of Iron Deficiency Anemia With Ferrous

2 Fumarate," Am. J. Obst. & Gynec., 203-206, 1962. Shapleigh, J.B., and Montgomery, A.; Am. Pract. &

3 Dig. Treat. 10-461, 1959. Brise, H. and Hallberg, L.: "Effect of Ascorbic Acid on Iron Absorption," Acta.

4 5 Med. Scand. 171 :376, 51 -58,1962. New Drugs, p. 309, AMA, Chicago, 1966. Mazur, A., Green, S. and Carleton, A.: "Mechanism of Plasma Iron Incorporation into Hepatic Ferritin," J. of Bio. Chem.

6 3:595-603, 1960. Greenberg, S.M., Tucker, A.E., Mathues, H. and J.D.: "Iron Absorption and

7 Metabolism, I. Interrelationship of Ascorbic Acid and Vitamin E," J. Nutrition 63:19-31, 1957. Moore, C. V., and Dubach, R.: "Observations on the Absorption of Iron From Foods Tagged with Radioiron,

8 "Trans. Assoc. Amer. Physic. 64:245, 1951. Steinkamp, R., Dubach, R. and Moore, C.Y. "Studies in

9 Iron Transportation and Metabolism," Arch. Int. Med. 95:181, 1955. Gorten, M.K. and Bradley, J.E.: "The Treatment of Nutritional Anemia in Infancy and Childhood with Oral Iron and Ascorbic

l0 Acid,"J. Pediatrics, 45: 1, 1954. Mazur, A.: "Role of Ascorbic Acid in the Incorporation of Plasma Iron

11 into Ferritin." An. N.Y. Acad. Sci. 92:223-229, 1961. COX, E. V. et al.: "The Anemia of Scurvy," Amer. J.

12 Med. 42:220-227, 1967. Berk, L. et al.: "Observations on the Etiologic Relationship of Achylia

13 Gastrica to Pernicious Anemia, X," N. Eng. J. Med. 239:911-913, 1948. Hall, B.E.: "Studies on the

14 Nature of the Intrinsic Factor of Castle," Brit. Med. J. 2:585-589,1950. Wallerstein, R.O. et al.: "Observations on the Etiologic Relationship of Achylia Gastrica to Pernicious Anemia, XV" J. Lab

15 & Clin. Med. 41 :363-375, 1953. Castle, W.B.: "Observations on the Etiologic Relationship of Achylia

16 Gastrica to Pernicious Anemia, 1," Am. J. Med. Sc.178:748-764, 1929.